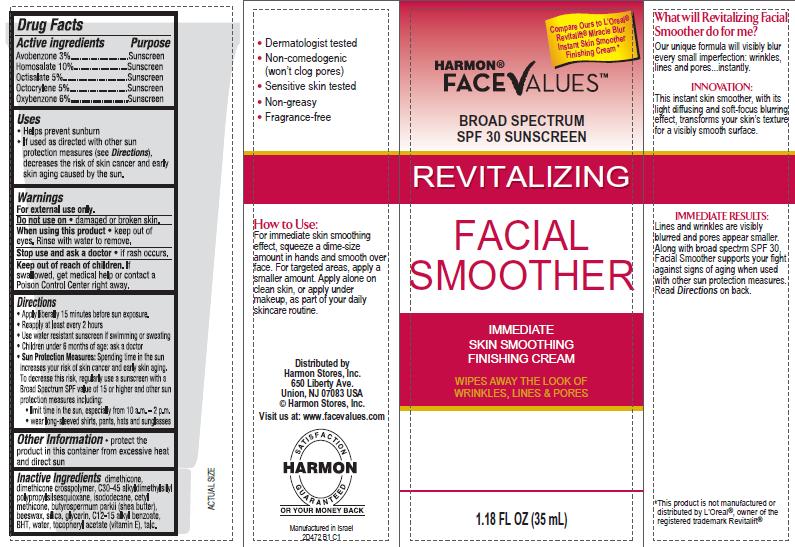 DRUG LABEL: Harmon Revitalizing Facial Smoother Immediate Skin Smoothing Finishing Broad Spectrum SPF30 Sunscreen
NDC: 63940-472 | Form: CREAM
Manufacturer: Harmon Stores Inc.
Category: otc | Type: HUMAN OTC DRUG LABEL
Date: 20140422

ACTIVE INGREDIENTS: AVOBENZONE 3 g/100 mL; HOMOSALATE 10 g/100 mL; OCTISALATE 5 g/100 mL; OCTOCRYLENE 5 g/100 mL; OXYBENZONE 6 g/100 mL
INACTIVE INGREDIENTS: DIMETHICONE; DIMETHICONE/DIENE DIMETHICONE CROSSPOLYMER; C30-45 ALKYL METHICONE; ISODODECANE; CETYL DIMETHICONE 45; SHEA BUTTER; YELLOW WAX; SILICON DIOXIDE; GLYCERIN; ALKYL (C12-15) BENZOATE; BUTYLATED HYDROXYTOLUENE; WATER; .ALPHA.-TOCOPHEROL ACETATE; TALC

Harmon Revitalizing Facial Smoother Immediate Skin Smoothing Finishing Broad Spectrum SPF30 Sunscreen

Active ingredient

Avobenzone 3%
Homosalate 10%
Octisalate 5%
Octocrylene 5%
Oxybenzone 6%

Purpose

Sunscreen

Uses

- Helps prevent sunburn
- If used as directed with other sun protection measures (see Directions), decreases the risk of skin cancer and early skin aging caused by the sun.

Warnings

For external use only.

Do not use on

- damaged or broken skin.

When using this product

- keep out of eyes. Rinse with water to remove.

Stop use and ask a doctor

- if rash occurs

Keep out of reach of children.

If swallowed, get medical help or contact a Poison Control Center right away.

Directions

- Apply liberally 15 minutes before sun exposure.
- Reapply at least every 2 hours
- Use water resistant sunscreen if swimming or sweating
- Children under 6 months of age: ask a doctor
- Sun Protection Measures: Spending time in the sun increases your risk of skin cancer and early skin aging. To decrease this risk, regularly use a sunscreen with a Broad Spectrum SPF value of 15 or higher and other sun protection measures including:
- limit time in the sun, especially from 10 a.m. – 2 p.m.
- wear long-sleeved shirts, pants, hats and sunglasses

Other Information

- protect the product in this container from excessive heat and direct sun

Inactive ingredients

dimethicone, dimethicone crosspolymer, C30-45 alkyldimethylsilyl polypropylsilsesquioxane, isododecane, cetyl methicone, butyrospermum parkii (shea butter), beeswax, silica, glycerin, C12-15 alkyl benzoate, BHT, water, tocopheryl acetate (vitamin E), talc.

Package/Label Principal Display Panel

HARMON®
FACEVALUES™

BROAD SEPECTRUM SPF 30 SUNSCREEN

REVITALIZING
FACIAL SMOOTHER

IMMEDIATE SKIN SMOOTHING FINISHING CREAM

WIPES AWAY THE LOOK OF WRINKLES, LINES & PORES

1.18 FL OZ (35 mL)

Compare Ours to L'Oreal® Revitalift® Miracle Blur Instant Skin Smoother Finishing Cream*

What will Revitalizing Facial Smoother do for me?

Our unique formula will visibly blur every small imperfection: wrinkles, lines and pores...instantly.

INNOVATION:

This instant skin smoother, with its light diffusing and soft-focus blurring effect, transforms your skin’s texture for a visibly smooth surface.

IMMEDIATE RESULTS:

Lines and wrinkles are visibly blurred and pores appear smaller. Along with broad spectrum SPF 30, Facial Smoother supports your ﬁght against signs of aging when used with other sun protection measures. Read Directions on back.

*This product is not manufactured or distributed by L'Oreal®, owner of the registered trademark Revitalift®

- Dermatologist tested
- Non-comedogenic (won’t clog pores)
- Sensitive skin tested
- Non-greasy
- Fragrance-free

How to Use:

For immediate skin smoothing effect, squeeze a dime-size amount in hands and smooth over face. For targeted areas, apply a smaller amount. Apply alone on clean skin, as part of your daily skincare routine.

Distributed by
Harmon Stores, Inc.
650 Liberty Ave.
Union, NJ 07083 USA
© Harmon Stores, Inc.
Visit us at: www.facevalues.com

HARMON SATISFACTION GUARANTEED
OR YOUR MONEY BACK

Manufactured in Israel
2D472 B1 C1

Carton Label